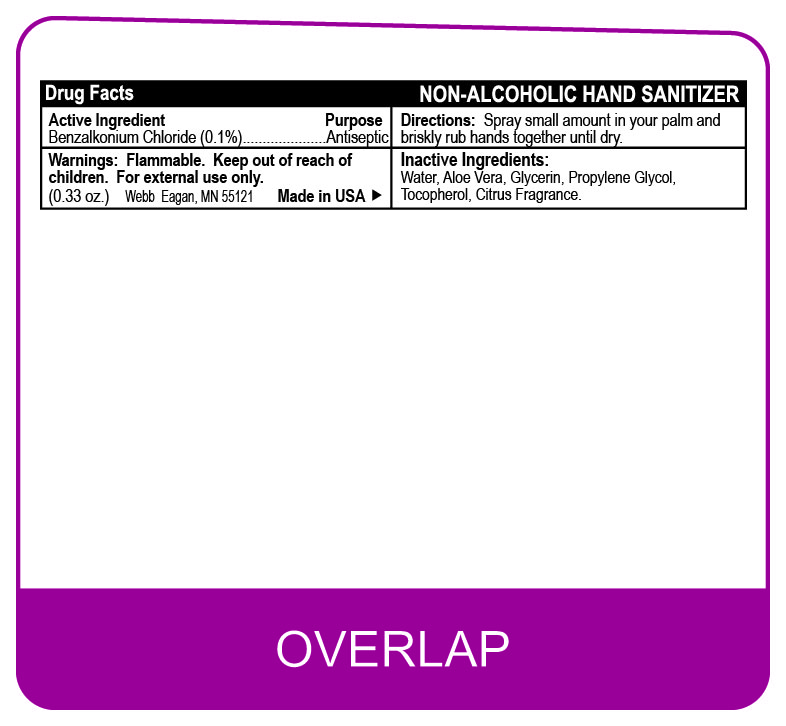 DRUG LABEL: Antibacterial Hand Sanitizer
NDC: 70445-420 | Form: SPRAY
Manufacturer: Webb Business Promotions, Inc
Category: otc | Type: HUMAN OTC DRUG LABEL
Date: 20220104

ACTIVE INGREDIENTS: BENZALKONIUM CHLORIDE 1 mg/100 mL
INACTIVE INGREDIENTS: GLYCERIN; PROPYLENE GLYCOL; WATER; TOCOPHEROL; ALOE VERA LEAF

Antibacterial Hand Sanitizer

Active Ingridient

Benzalkonium Chloride

Inactive Ingridients

Water, Aloe Vera, Glycerin, Propylene Glycol, Tocopherol

Purpose

Antiseptic

Keep out of reach of children

Warning

Flammable

DOSAGE AND ADMINISTRATION

Spray small ammount in your palm and briskly rub hands together until dry.

OTHER SAFETY INFORMATION

For external use only

INDICATIONS AND USAGE

For external use only.

PACKAGE LABEL

NON-ALCOHOLIC HAND SANITIZER